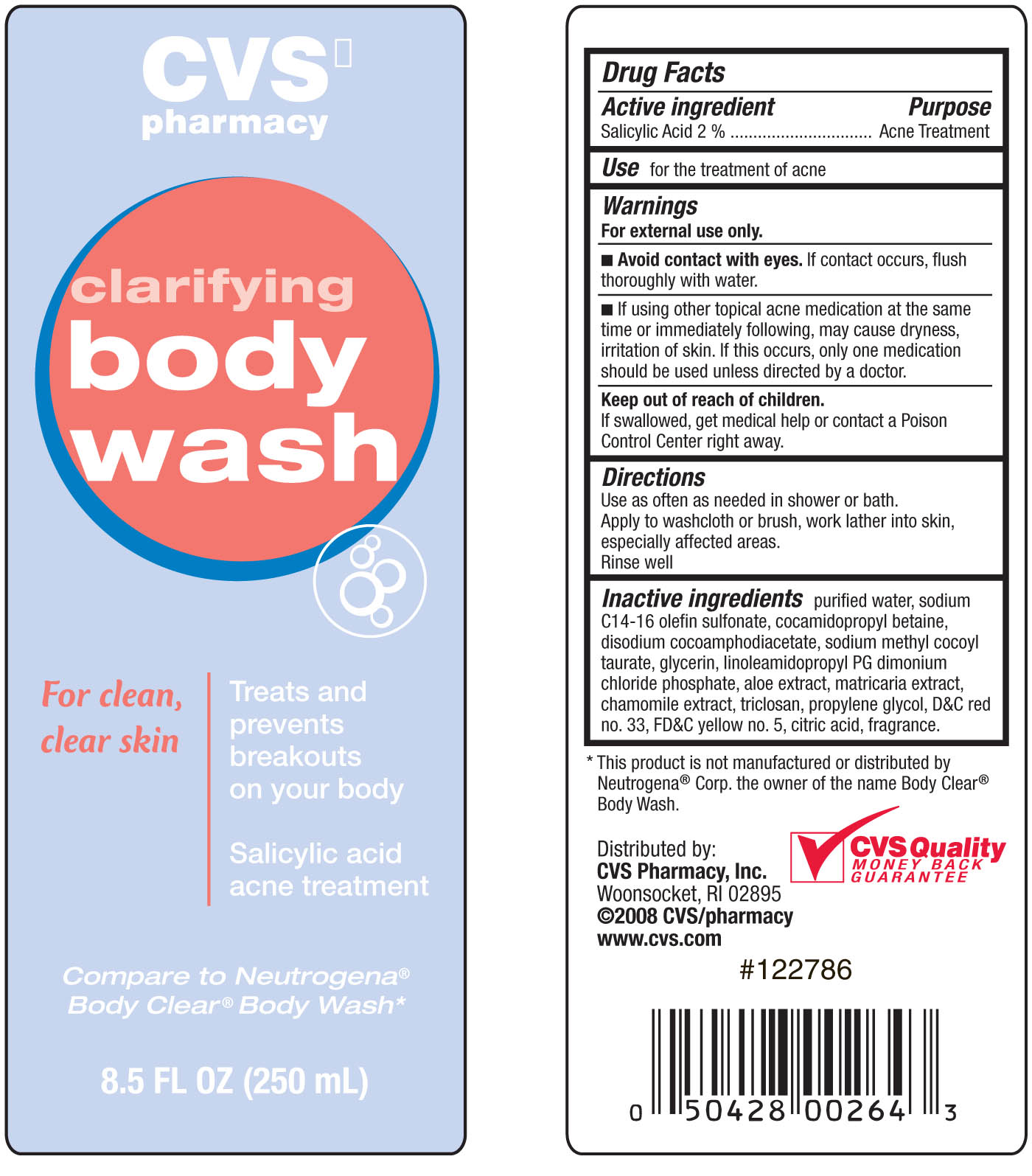 DRUG LABEL: CVS Clarifying Body Wash
NDC: 59779-073 | Form: SOAP
Manufacturer: CVS Pharmacy
Category: otc | Type: HUMAN OTC DRUG LABEL
Date: 20100710

ACTIVE INGREDIENTS: SALICYLIC ACID 20 mg/1 mL
INACTIVE INGREDIENTS: WATER; SODIUM C14-16 OLEFIN SULFONATE; PROPYLENE GLYCOL; CETYL BETAINE; GLYCERIN; ALOE VERA LEAF; MATRICARIA RECUTITA; TRICLOSAN; CITRIC ACID MONOHYDRATE; D&C RED NO. 33; FD&C YELLOW NO. 5

drug facts

Active ingredients Purpose
Salicylic Acid 2%............................................Acne Treatment

Uses
- for the treatment of acne

Keep out of reach of children. If swallowed, get medical help or contact
a Poison Control Center right away.

Uses
- for the treatment of acne

Warnings
For external use only.
- Avoid contact with eyes. If contact occurs, flush thoroughly with water.
- if using other topical acne medication at the same time or immediately following,
may cause dryness, irritation of skin. If this occurs, only one medication should
be used unless directed by a doctor.
Keep out of the reach of children. If swallowed, get medical help or contact a Poison Control Center right away

Directions
Use as often as needed in shower or bath. Apply to washcloth or brush,
work lather into skin, especially affected areas. Rinse well

INACTIVE INGREDIENT

Inactive Ingredients purified water, sodium C14-16 olefin sulfonate, cocamidopropyl betaine,
disodium cocoamphodiacetate, sodium methyl cocoyl taurate, glycerin, linoeamidopropyl PG
dimonium chloride phosphate, aloe extract, matricaria extract, chamomile extract, triclosan,
propylene glycol, DandC red no.33, FDandC yellow no. 5, citric acid, fragrance